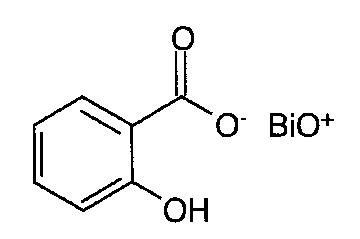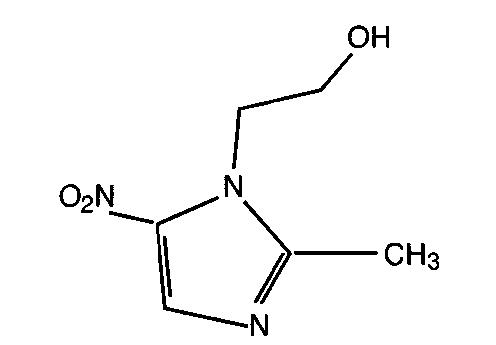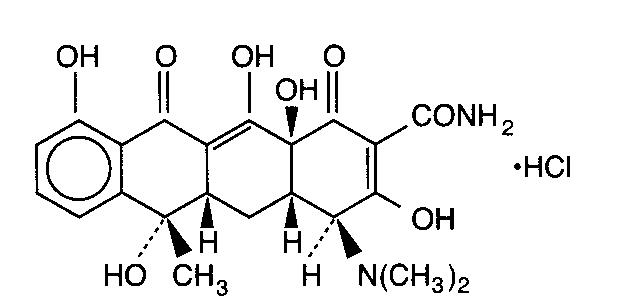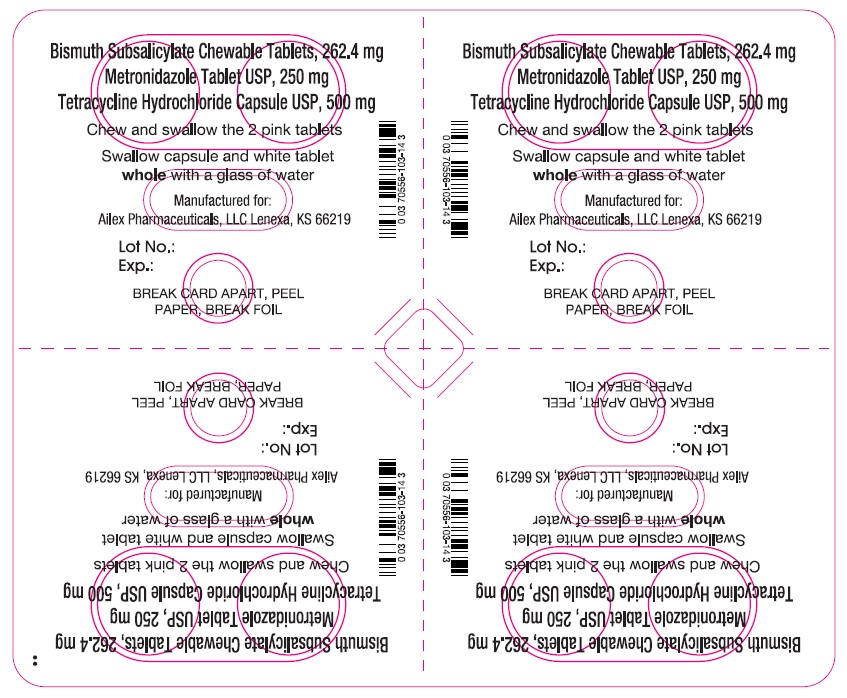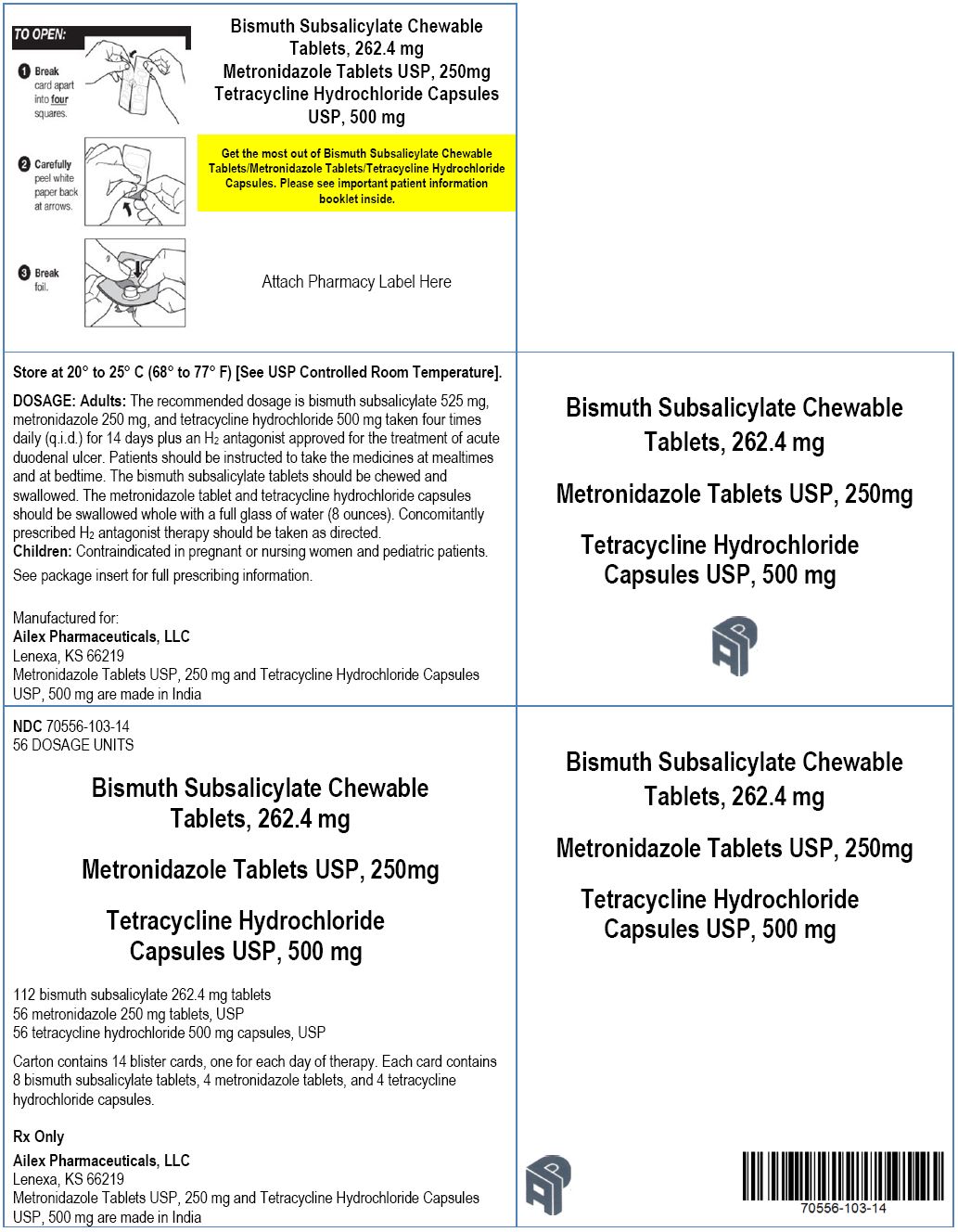 DRUG LABEL: Bismuth Subsalicylate/Metronidazole/Tetracycline Hydrochloride
NDC: 70556-103 | Form: KIT | Route: ORAL
Manufacturer: Ailex Pharmaceuticals, LLC
Category: prescription | Type: HUMAN PRESCRIPTION DRUG LABEL
Date: 20191124

ACTIVE INGREDIENTS: BISMUTH SUBSALICYLATE 262.4 mg/1 1; METRONIDAZOLE 250 mg/1 1; TETRACYCLINE HYDROCHLORIDE 500 mg/1 1
INACTIVE INGREDIENTS: CALCIUM CARBONATE; D&C RED NO. 27 ALUMINUM LAKE; MAGNESIUM STEARATE; MANNITOL; POVIDONE; SACCHARIN SODIUM; TALC; SILICON DIOXIDE; HYDROXYPROPYL CELLULOSE (1600000 WAMW); ANHYDROUS LACTOSE; CELLULOSE, MICROCRYSTALLINE; SODIUM STARCH GLYCOLATE TYPE A POTATO; STEARIC ACID; LACTOSE; MAGNESIUM STEARATE; SODIUM LAURYL SULFATE; FD&C BLUE NO. 1; FD&C RED NO. 40; GELATIN; TITANIUM DIOXIDE; BENZYL ALCOHOL; BUTYLPARABEN; EDETATE CALCIUM DISODIUM; FD&C YELLOW NO. 6; METHYLPARABEN; PROPYLPARABEN; SILICON DIOXIDE; SODIUM PROPIONATE; DIMETHICONE; WATER; ALCOHOL; ETHYLENE GLYCOL MONOETHYL ETHER; SHELLAC; LECITHIN, SOYBEAN

Bismuth Subsalicylate Chewable Tablets/Metronidazole Tablets/Tetracycline Hydrochloride Capsules

PRODUCTS ARE INTENDED ONLY FOR USE AS DESCRIBED. The individual products contained in this package should not be used alone or in combination for other purposes. The information described in this labeling concerns only the use of these products as indicated in this combination package. For information on use of the individual components when dispensed as individual medications outside this combined use for treating Helicobacter pylori, please see the package inserts for each individual product.

WARNING: POTENTIAL FOR CARCINOGENICITY

Metronidazole has been shown to be carcinogenic in mice and rats. It is unknown whether metronidazole is associated with carcinogenicity in humans (see WARNINGS).

DESCRIPTION:

Bismuth Subsalicylate Chewable Tablets/Metronidazole Tablets/Tetracycline Hydrochloride Capsules consists of 112 bismuth subsalicylate 262.4-mg chewable tablets, 56 metronidazole 250-mg tablets, USP, and 56 tetracycline hydrochloride 500-mg capsules, USP, for oral administration.

Bismuth subsalicylate chewable tablets: Each pink round tablet contains 262.4 mg bismuth subsalicylate (102 mg salicylate) for oral administration.

Bismuth subsalicylate is a fine, white, odorless, and tasteless powder that is stable and non-hygroscopic. It is a highly insoluble salt of trivalent bismuth and salicylic acid.

Bismuth subsalicylate is 2-Hydroxybenzoic acid bismuth (3+) salt with the following structural formula:

Molecular weight: 362.11

Inactive Ingredients: Each bismuth subsalicylate chewable tablet contains calcium carbonate, D&C Red No. 27 aluminum lake, magnesium stearate, mannitol, povidone, saccharin sodium, talc, and wintergreen flavor.

Metronidazole tablets, USP: Each round, white tablet contains 250 mg metronidazole. Metronidazole is 2Methyl-5-nitroimidazole-1-ethanol, with the following structural formula:

Molecular weight: 171.16

Inactive Ingredients: Each metronidazole tablet contains colloidal silicon dioxide, hydroxypropyl cellulose, lactose (anhydrous), sodium starch glycolate, stearic acid, and microcrystalline cellulose.

Tetracycline hydrochloride capsules, USP: Each black and yellow capsule contains 500 mg tetracycline hydrochloride. Tetracycline is a yellow, odorless, crystalline powder. Tetracycline is stable in air but exposure to strong sunlight causes it to darken. Its potency is affected in solutions of pH below 2 and is rapidly destroyed by alkali hydroxide solutions. Tetracycline is very slightly soluble in water, freely soluble in dilute acid and in alkali hydroxide solutions, sparingly soluble in alcohol, and practically insoluble in chloroform and ether.

Tetracycline hydrochloride is (4S,4aS,5aS,6S,12aS)-4-(Dimethylamino)-1,4,4a,5,5a,6,11,12a-octahydro3,6,10,12,12a-pentahydroxy-6-methyl-1,11-dioxo-2-naphthacenecarboxamide monohydrochloride, with the following structural formula:

Molecular weight: 480.90

Inactive Ingredients: Each tetracycline hydrochloride capsule contains lactose, magnesium stearate and sodium lauryl sulfate; D & C yellow no.10, FD & C blue No 1, FD & C red no. 40, gelatin and titanium dioxide. It may also contain benzyl alcohol, butylparaben, edetate calcium disodium, FD & C yellow no. 6, methylparaben, propylparaben, silicon dioxide and sodium propionate.

The imprinting ink for tetracycline hydrochloride capsule contains titanium dioxide. It may also contain dimethyl polysiloxane, distilled water, ethyl alcohol, ethylene glycol monoethyl ether, pharmaceutical glaze, pharmaceutical shellac, and soya lecithin.

CLINICAL PHARMACOLOGY

PHARMACOKINETICS

Pharmacokinetics: Pharmacokinetics for Bismuth Subsalicylate Chewable Tablets/ Metronidazole Tablets/Tetracycline Hydrochloride Capsules components (bismuth subsalicylate chewable tablets, metronidazole tablets, and tetracycline hydrochloride capsules) when coadministered has not been studied. There is no information about the gastric mucosal concentrations of bismuth, metronidazole, and tetracycline after administration of these agents concomitantly or in combination with an acid suppressive agent. The systemic pharmacokinetic information presented below is based on studies in which each product was administered alone.

Bismuth Subsalicylate: Upon oral administration, bismuth subsalicylate is almost completely hydrolyzed in the gastrointestinal tract to bismuth and salicylic acid. Thus, the pharmacokinetics of bismuth subsalicylate following oral administration can be described by the individual pharmacokinetics of bismuth and salicylic acid.

Bismuth: Less than 1% of bismuth from oral doses of bismuth subsalicylate is absorbed from the gastrointestinal tract into the systemic circulation. Absorbed bismuth is distributed throughout the body. Bismuth is highly bound to plasma proteins (> 90%). Bismuth has multiple disposition half-lives with an intermediate half-life of 5 to 11 days and a terminal half-life of 21 to 72 days. Elimination of bismuth is primarily through urinary and biliary routes with a renal clearance of 50 ± 18 mL/min. The mean trough blood bismuth concentration after 2 weeks oral administration of 787 mg bismuth subsalicylate (3 chewable tablets) four times daily under fasted condition was 5.1 ± 3.1 ng/mL. In another study, the mean trough blood bismuth concentration after 2 weeks oral administration of 525 mg bismuth subsalicylate (as PEPTO-BISMOL® liquid suspension) four times daily was 5 ng/mL with the highest value being 32 ng/mL.

Salicylic Acid: More than 80% of the salicylic acid is absorbed from oral doses of bismuth subsalicylate chewable tablets. Salicylic acid is about 90% plasma protein bound. The volume of distribution is about 170 mL/kg of body weight. Salicylic acid is extensively metabolized and about 10% is excreted unchanged in the urine. The metabolic clearance of salicylic acid is saturable; accordingly, nonlinear pharmacokinetics is observed at bismuth subsalicylate doses above 525 mg. Salicylic acid metabolic clearance is lower in females than in males. The terminal half-life of salicylic acid upon a single oral dose of 525 mg bismuth subsalicylate is between 2 to 5 hours. After a single oral dose of 525 mg bismuth subsalicylate (2 chewable tablets), the mean peak plasma salicylic acid concentration was 13.1 ± 3.4 mcg/mL under fasted condition. The mean steady-state serum total salicylate concentration after 2 weeks oral administration of 525 mg bismuth subsalicylate (as PEPTO-BISMOL liquid suspension) four times daily was 24 mcg/mL with the highest value being 70 mcg/mL.

Metronidazole: Following oral administration, metronidazole is well absorbed, with peak plasma concentrations occurring between 1 and 2 hours after administration. Plasma concentrations of metronidazole are proportional to the administered dose, with oral administration of 250 mg producing a peak plasma concentration of 6 mcg/mL. Studies reveal no significant bioavailability differences between males and females; however because of weight differences, the resulting plasma levels in males are generally lower.

Metronidazole is the major component appearing in the plasma, with lesser quantities of the 2hydroxymethyl metabolite also being present. Less than 20% of the circulating metronidazole is bound to plasma proteins. Metronidazole also appears in cerebrospinal fluid, saliva, and human milk in concentrations similar to those found in plasma.

The average elimination half-life in normal volunteers is 8 hours. The major route of elimination of metronidazole and its metabolites is via the urine (60% to 80% of the dose), with fecal excretion accounting for 6% to 15% of the dose. The metabolites that appear in the urine result primarily from side-chain oxidation [1-(ß-hydroxyethyl)-2-hydroxymethyl-5-nitroimidazole and 2-methyl-5-nitroimidazole-1yl-acetic acid] and glucuronide conjugation, with unchanged metronidazole accounting for approximately 20% of the total. Renal clearance of metronidazole is approximately 10 mL/min/1.73 m^2.

Decreased renal function does not alter the single-dose pharmacokinetics of metronidazole. In patients with decreased liver function, plasma clearance of metronidazole is decreased.

Tetracycline Hydrochloride: Tetracycline hydrochloride is absorbed (60%-90%) in the stomach and upper small intestine. The presence of food, milk or cations may significantly decrease the extent of absorption. In the plasma, tetracycline is bound to plasma proteins in varying degrees. It is concentrated by the liver in the bile and excreted in the urine and feces at high concentrations in biologically active form. Tetracycline hydrochloride is distributed into most body tissues and fluids. It is distributed into the bile and undergoes varying degrees of enterohepatic recirculation. Tetracycline hydrochloride tends to localize in tumors, necrotic or ischemic tissue, liver and spleen and form tetracycline-calcium orthophosphate complexes at sites of new bone formation or tooth development. Tetracycline readily crosses the placenta and is excreted in high amounts in breast milk (see WARNINGS and PRECAUTIONS, Nursing Mothers). Tetracyclines are readily absorbed and are bound to plasma proteins in varying degrees. They are concentrated by the liver in the bile and excreted in the urine and feces at high concentrations in a biologically active form.

The relative contribution of systemic versus local antimicrobial activity against H. pylori for agents used in eradication therapy has not been established.

Microbiology:
Mechanism of Action
Bismuth Subsalicylate Chewable Tablets/Metronidazole Tablets/Tetracycline Hydrochloride Capsules is a combination of antibacterial agents (metronidazole and tetracycline hydrochloride) and bismuth subcitrate potassium. Tetracycline hydrochloride interacts with the 30S subunit of the bacterial ribosome and inhibits protein synthesis. Metronidazole's antibacterial mechanism of action in an anaerobic environment is not fully understood but a possible mechanism includes reduction by intracellular electron transport proteins after entry into the organism. Because of this alteration to the metronidazole molecule, a concentration gradient is created and maintained which promotes the drugs intracellular transport. Presumably, free radicals are formed which, in turn, react with cellular components resulting in death of bacteria. The antibacterial action of bismuth salts is not well understood.

Activity In Vitro and In Vivo
Bismuth Subsalicylate Chewable Tablets/Metronidazole Tablets/Tetracycline Hydrochloride Capsules has been shown to be active against most isolates of Helicobacter pylori both in vitro, and in clinical infections as described in the CLINICAL STUDIES and INDICATIONS AND USAGE sections.

Susceptibility Testing
For specific information regarding susceptibility test interpretive criteria and associated test methods and quality control standards recognized by FDA for this drug, please see: https://www.fda.gov/STIC.

INDICATIONS AND USAGE:

The components of Bismuth Subsalicylate Chewable Tablets/ Metronidazole Tablets/Tetracycline Hydrochloride Capsules (bismuth subsalicylate, metronidazole, and tetracycline hydrochloride), in combination with an H2 antagonist, are indicated for the eradication of H. pylori for treatment of patients with H. pylori infection and duodenal ulcer disease (active or a history of duodenal ulcer). The eradication of H. pylori has been demonstrated to reduce the risk of duodenal ulcer recurrence in patients with active duodenal ulcer disease (see CLINICAL STUDIES and DOSAGE AND ADMINISTRATION).

To reduce the development of drug-resistant bacteria and maintain the effectiveness of Bismuth Subsalicylate Chewable Tablets/Metronidazole Tablets/Tetracycline Hydrochloride Capsules and other antibacterial drugs, Bismuth Subsalicylate Chewable Tablets/Metronidazole Tablets/Tetracycline Hydrochloride Capsules should be used only to treat or prevent infections that are proven or strongly suspected to be caused by susceptible bacteria. When culture and susceptibility information are available, they should be considered in selecting or modifying antibacterial therapy. In the absence of such data, local epidemiology and susceptibility patterns may contribute to the empiric selection of therapy.

CONTRAINDICATIONS:

Methoxyflurane
Do not administer methoxyflurane to patients taking Bismuth Subsalicylate Chewable Tablets/Metronidazole Tablets/Tetracycline Hydrochloride Capsules. The concurrent use of tetracycline hydrochloride, a component of Bismuth Subsalicylate Chewable Tablets/Metronidazole Tablets/Tetracycline Hydrochloride Capsules with methoxyflurane has been reported to result in fatal renal toxicity (see DRUG INTERACTIONS).

Disulfiram
Bismuth Subsalicylate Chewable Tablets/Metronidazole Tablets/Tetracycline Hydrochloride Capsules is contraindicated in patients who have taken disulfiram within the last two weeks. Psychotic reactions have been reported in alcoholic patients who are using metronidazole, a component of Bismuth Subsalicylate Chewable Tablets/Metronidazole Tablets/Tetracycline Hydrochloride Capsules and disulfiram concurrently (see DRUG INTERACTIONS).

Alcohol
Alcoholic beverages or other products containing propylene glycol should not be consumed during and for at least 3 days after usage of Bismuth Subsalicylate Chewable Tablets/Metronidazole Tablets/Tetracycline Hydrochloride Capsules. A disulfiram-like reaction (abdominal cramps, nausea, vomiting, headaches, and flushing) may occur due to the interaction between alcohol or propylene glycol and metronidazole, a component of Bismuth Subsalicylate Chewable Tablets/Metronidazole Tablets/Tetracycline Hydrochloride Capsules (see DRUG INTERACTIONS).

Renal Impairment
Bismuth Subsalicylate Chewable Tablets/Metronidazole Tablets/Tetracycline Hydrochloride Capsules is contraindicated in patients with severe renal impairment. The antianabolic action of the tetracyclines may cause an increase in blood urea nitrogen (BUN) (see ADVERSE REACTIONS). In patients with significantly impaired renal function, higher serum concentrations of tetracyclines may lead to azotemia, hyperphosphatemia, and acidosis.

Hypersensitivity Reactions
Bismuth Subsalicylate Chewable Tablets/Metronidazole Tablets/Tetracycline Hydrochloride Capsules is contraindicated in patients with known hypersensitivity (e.g. urticaria, erythematous rash, flushing, and fever) to bismuth subsalicylate, metronidazole or other nitroimidazole derivatives, or tetracycline (see ADVERSE REACTIONS).

Allergy to Aspirin or other Salicylates
Bismuth Subsalicylate Chewable Tablets/Metronidazole Tablets/Tetracycline Hydrochloride Capsules should not be administered to those patients who have a known allergy to aspirin or salicylates.

WARNINGS:

Potential for Carcinogenicity

Metronidazole has been shown to be carcinogenic in mice and rats. Tumors affecting the liver, lungs, mammary and lymphatic tissues have been detected in several studies of metronidazole in rats and mice, but not hamsters (see PRECAUTIONS, Carcinogenesis, Mutagenesis, Impairment of Fertility). It is unknown whether metronidazole is associated with carcinogenicity in humans.

Fetal Toxicity

There are no adequate and well-controlled studies of Bismuth Subsalicylate Chewable Tablets/Metronidazole Tablets/Tetracycline Hydrochloride Capsules in pregnant women. However, tetracycline can cause fetal harm when administered to a pregnant woman. The use of drugs of the tetracycline class during the second and third trimester of pregnancy can also cause permanent discoloration of the teeth (yellow-gray brown) and possibly inhibit bone development (See WARNINGS). Administration of oral tetracycline to pregnant rats at various doses resulted in yellow fluorescence in teeth and bones in the newborn animals. Metronidazole usage in pregnancy has been evaluated in numerous studies. In one of these studies, an increased risk of cleft lip, with or without cleft palate, was noted in infants exposed to metronidazole in–utero; however these findings were not confirmed. If Bismuth Subsalicylate Chewable Tablets/Metronidazole Tablets/Tetracycline Hydrochloride Capsules is used during pregnancy, or if the patient becomes pregnant while taking Bismuth Subsalicylate Chewable Tablets/Metronidazole Tablets/Tetracycline Hydrochloride Capsules, the patient should be apprised of the potential hazard to the fetus (see PRECAUTIONS, Pregnancy).

Maternal Toxicity

Tetracycline administered during pregnancy at high doses (> 2 g IV) was associated with rare but serious cases of maternal hepatotoxicity. This syndrome may result in stillborn or premature birth due to maternal pathology (see PRECAUTIONS).

Tooth Enamel Discoloration and Hypoplasia

The use of drugs of the tetracycline class during tooth development (last half of pregnancy, infancy, and childhood to the age of 8 years) may cause permanent discoloration of the teeth (yellow-gray-brown). This adverse reaction is more common during long-term use of the drug, but has been observed following repeated short-term courses. Enamel hypoplasia has also been reported. Bismuth Subsalicylate Chewable Tablets/Metronidazole Tablets/Tetracycline Hydrochloride Capsules, therefore, should not be used in this age group unless other drugs are not likely to be effective or are contraindicated (see PRECAUTIONS).

Central and Peripheral Nervous System Effects

Metronidazole: Cases of convulsive seizures, encephalopathy and peripheral neuropathy (including optic neuropathy) have been reported with metronidazole. Encephalopathy has been reported in association with cerebellar toxicity characterized by ataxia, dizziness, and dysarthria. CNS lesions seen on MRI have been described in reports of encephalopathy. CNS symptoms are generally reversible within days to weeks upon discontinuation of metronidazole. CNS lesions seen on MRI have also been described as reversible. Peripheral neuropathy, mainly of sensory type has been reported and is characterized by numbness or paresthesia of an extremity. Cases of aseptic meningitis have been reported with metronidazole. Symptoms can occur within hours of dose administration and generally resolve after metronidazole therapy is discontinued.

Tetracycline: Intracranial hypertension (IH, pseudotumor cerebri) has been associated with the use of tetracyclines. Clinical manifestations of IH include headache, blurred vision, diplopia, and vision loss; papilledema can be found on fundoscopy. Women of childbearing age who are overweight or have a history of IH are at greater risk for developing tetracycline associated IH. Concomitant use of isotretinoin should be avoided because isotretinoin is also known to cause IH.

Although IH typically resolves after discontinuation of treatment, the possibility for permanent visual loss exists. If visual disturbance occurs during treatment, prompt ophthalmologic evaluation is warranted. Since intracranial pressure can remain elevated for weeks after drug cessation, patients should be monitored until they stabilize.

Bismuth-containing products: Cases of neurotoxicity associated with excessive doses of various bismuth-containing products, including bismuth subsalicylate have been reported. Effects have been reversible with discontinuation of therapy.

The appearance of abnormal neurologic signs and symptoms demands the prompt evaluation of the benefit/risk ratio of the continuation of therapy (see ADVERSE REACTIONS).

Risk of Reye’s syndrome

Use of Bismuth Subsalicylate Chewable Tablets/Metronidazole Tablets/Tetracycline Hydrochloride Capsules is not recommended in children and teenagers who have or who are recovering from varicella (chicken pox) or influenza due to the risk of Reye’s syndrome, a rare but serious illness. If Bismuth Subsalicylate Chewable Tablets/Metronidazole Tablets/Tetracycline Hydrochloride Capsules is used in this population and nausea or vomiting is present, patients are advised to consult a doctor because this could be an early sign of Reye’s syndrome.

Cutaneous Reactions

Skin and subcutaneous disorders including Stevens-Johnson syndrome, toxic epidermal necrolysis and DRESS syndrome (drug rash with eosinophilia and systemic symptoms) have been reported. Discontinue treatment at the first evidence of a cutaneous reaction (see ADVERSE REACTIONS).

PRECAUTIONS:

Development of Superinfections

Known or previously unrecognized candidiasis may present more prominent symptoms during therapy with metronidazole and requires treatment with an antifungal agent.

As with other antibiotics, use of tetracycline hydrochloride may result in overgrowth of nonsusceptible organisms, including fungi. If superinfection occurs discontinue Bismuth Subsalicylate Chewable Tablets/Metronidazole Tablets/Tetracycline Hydrochloride Capsules and institute appropriate therapy.

Photosensitivity

Photosensitivity manifested by an exaggerated sunburn reaction has been observed in some individuals taking tetracyclines (see ADVERSE REACTIONS). Patients apt to be exposed to direct sunlight or ultraviolet light should be advised that this reaction can occur with tetracycline drugs. Instruct patients taking Bismuth Subsalicylate Chewable Tablets/Metronidazole Tablets/Tetracycline Hydrochloride Capsules to avoid exposure to the sun or sun lamps. Treatment should be discontinued at the first evidence of skin erythema.

Darkening of the Tongue and/or Black Stool

Bismuth subsalicylate may cause a temporary and harmless darkening of the tongue and/or black stool, generally reversible within several days after treatment is stopped (see ADVERSE REACTIONS). Stool darkening should not be confused with melena.

Use in Patients with Blood Dyscrasias

BMetronidazole is a nitroimidazole and should be used with caution in patients with evidence of, or history of, blood dyscrasia. A mild leukopenia has been observed during its administration; however, no persistent hematologic abnormalities attributable to metronidazole have been observed in clinical studies. Total and differential leukocyte counts are recommended before and after therapy (see ADVERSE REACTIONS).

Increased Plasma Concentrations in Patients with Hepatic Impairment

Patients with hepatic impairment metabolize metronidazole slowly, with resultant accumulation of metronidazole in the plasma. Use Bismuth Subsalicylate Chewable Tablets/Metronidazole Tablets/Tetracycline Hydrochloride Capsules with caution in patients with mild to moderate hepatic impairment. Bismuth Subsalicylate Chewable Tablets/Metronidazole Tablets/Tetracycline Hydrochloride Capsules may not be appropriate for patients with severe hepatic impairment (Child-Pugh C) (see DOSAGE AND ADMINISTRATION and CLINICAL PHARMACOLOGY).

Laboratory Test Interactions

Bismuth absorbs x-rays and may interfere with x-ray diagnostic procedures of the gastrointestinal tract.

Bismuth subsalicylate may cause a temporary and harmless darkening of the stool. However, this change does not interfere with standard tests for occult blood.

Metronizadole may interfere with certain types of determinations of serum chemistry values, such as aspartate aminotransferase (AST, SGOT), alanine aminotransferase (ALT, SGPT), lactate dehydrogenase (LDH), triglycerides, and hexokinase glucose. Values of zero may be observed. All of the assays in which interference has been reported involve enzymatic coupling of the assay to oxidation-reduction of nicotinamide (NAD+ <=> NADH). Interference is due to the similarity in absorbance peaks of NADH (340 nm) and metronidazole (322 nm) at pH 7.

Development of Drug Resistant Bacteria

Prescribing Bismuth Subsalicylate Chewable Tablets/Metronidazole Tablets/Tetracycline Hydrochloride Capsules in the absence of a proven or strongly suspected bacterial infection or a prophylactic indication is unlikely to provide benefit to the patient and increases the risk of the development of drug-resistant bacteria.

INFORMATION FOR PATIENTS:

Pregnant Women

Advise pregnant women that Bismuth Subsalicylate Chewable Tablets/Metronidazole Tablets/Tetracycline Hydrochloride Capsules can cause fetal harm. Tetracycline use during the second and third trimesters of pregnancy can cause permanent discoloration of the teeth (yellow-gray brown) and may inhibit bone development and metronidazole has been shown in one study to increase the risk of cleft lip with or without cleft palate (see WARNINGS).

Human Milk Feeding

Advise women to avoid feeding their infants with their milk during Bismuth Subsalicylate Chewable Tablets/Metronidazole Tablets/Tetracycline Hydrochloride Capsules therapy. Women should either discontinue feeding or pump and discard their milk during treatment and for 24 hours after the last dose (see PRECAUTIONS, Nursing Mothers).

Hypersensitivity

Inform patients that Bismuth Subsalicylate Chewable Tablets/Metronidazole Tablets/Tetracycline Hydrochloride Capsules may cause allergic reactions and to discontinue Bismuth Subsalicylate Chewable Tablets/Metronidazole Tablets/Tetracycline Hydrochloride Capsules at the first sign of urticaria, erythematous rash, flushing, and fever or other symptoms of an allergic reaction (see CONTRAINDICATIONS).

Central Nervous System Effects

Inform patients of the risk of central and peripheral nervous system effects with Bismuth Subsalicylate Chewable Tablets/Metronidazole Tablets/Tetracycline Hydrochloride Capsules and to discontinue Bismuth Subsalicylate Chewable Tablets/Metronidazole Tablets/Tetracycline Hydrochloride Capsules and report immediately to their health-care provider if any neurologic symptoms occur (see WARNINGS).

Photosensivity

Avoid exposure to sun or sun lamps while taking Bismuth Subsalicylate Chewable Tablets/Metronidazole Tablets/Tetracycline Hydrochloride Capsules (see PRECAUTIONS).

Photosensivity

Patients should be advised to report to their doctor the use of any other medications while taking Bismuth Subsalicylate Chewable Tablets/Metronidazole Tablets/Tetracycline Hydrochloride Capsules. The administration of any of the following drugs with Bismuth Subsalicylate Chewable Tablets/Metronidazole Tablets/Tetracycline Hydrochloride Capsules may result in clinically significant adverse reactions or insufficient drug efficacies (see CONTRAINDICATIONS, WARNINGS, PRECAUTIONS, and DRUG INTERACTIONS).

• Methoxyflurane
• Disulfiram
• Alcoholic Beverages, or Products Containing Propylene Glycol
• Oral Contraceptives
• Anticoagulants
• Lithium
• Antacids, Multivitamins, or Dairy Products
• Antidiabetic agents
• Aspirin
• Probenecid or Sulfinpyrazone
• Cimetidine
• Phenytoinor Phenobarbital

Darkening of the Tongue and/or Stool

Bismuth Subsalicylate Chewable Tablets/Metronidazole Tablets/Tetracycline Hydrochloride Capsules may cause temporary and harmless darkening of the tongue and/or black stool and is generally reversible within several days after treatment is stopped. Stool darkening should not be confused with melena (blood in the stool) (see PRECAUTIONS).

Dosing and Administration Information

Each dose includes 4 pills: 2 pink round chewable tablets (bismuth subsalicylate), 1 white round tablet (metronidazole), and 1 black and yellow capsule (tetracycline hydrochloride). Each dose (all 4 pills) should be taken 4 times a day, at mealtimes and bedtime. Patients should be instructed to chew and swallow the pink round tablets (bismuth subsalicylate tablets) and to swallow the white round tablet (metronidazole tablet) and the black and yellow capsule (tetracycline hydrochloride capsule) whole with a full glass of water (8 ounces). Concomitantly prescribed H2 antagonist therapy should be taken as directed.

Missed doses can be made up by continuing the normal dosing schedule until the medication is gone. Patients should not take double doses. (If more than 4 doses are missed, the prescriber should be contacted (see DOSAGE AND ADMINISTRATION).

Salicylate Toxicity

Bismuth Subsalicylate Chewable Tablets/Metronidazole Tablets/Tetracycline Hydrochloride Capsules contains salicylates. If taken with aspirin and ringing in the ears occurs, the prescriber should be consulted concerning discontinuation of the aspirin therapy until the Bismuth Subsalicylate Chewable Tablets/Metronidazole Tablets/Tetracycline Hydrochloride Capsules therapy is completed (see OVERDOSAGE, WARNINGS, and DRUG INTERACTIONS).

Antibacterial Resistance

Patients should be counseled that antibacterial drugs, including Bismuth Subsalicylate Chewable Tablets/Metronidazole Tablets/Tetracycline Hydrochloride Capsules, should only be used to treat bacterial infections. They do not treat viral infections (e.g., the common cold). When Bismuth Subsalicylate Chewable Tablets/Metronidazole Tablets/Tetracycline Hydrochloride Capsules is prescribed to treat a bacterial infection, patients should be told that although it is common to feel better early in the course of therapy, the medication should be taken exactly as directed. Skipping doses or not completing the full course of therapy may (1) decrease the effectiveness of the immediate treatment and
(2) increase the likelihood that bacteria will develop resistance and will not be treatable by Bismuth Subsalicylate Chewable Tablets/Metronidazole Tablets/Tetracycline Hydrochloride Capsules or other antibacterial drugs in the future.

DRUG INTERACTIONS:

Methoxyflurane

Do not administer methoxyflurane to patients taking Bismuth Subsalicylate Chewable Tablets/Metronidazole Tablets/Tetracycline Hydrochloride Capsules. The concurrent use of tetracycline hydrochloride, a component of Bismuth Subsalicylate Chewable Tablets/Metronidazole Tablets/Tetracycline Hydrochloride Capsules, with methoxyflurane has been reported to result in fatal renal toxicity (see CONTRAINDICATIONS).

Disulfiram

Psychotic reactions have been reported in alcoholic patients who are using metronidazole and disulfiram concurrently. Bismuth Subsalicylate Chewable Tablets/ Metronidazole Tablets/Tetracycline Hydrochloride Capsules should not be given to patients who have taken disulfiram within the last 2 weeks (see CONTRAINDICATIONS).

Alcohol

Consumption of alcoholic beverages or administration of other products containing propylene glycol during treatment with Bismuth Subsalicylate Chewable Tablets/Metronidazole Tablets/Tetracycline Hydrochloride Capsules and for at least 3 days afterwards may cause a disulfiram-like reaction (abdominal cramps, nausea, vomiting, headaches, and flushing) due to the interaction between alcohol or propylene glycol and metronidazole, a component of Bismuth Subsalicylate Chewable Tablets/Metronidazole Tablets/Tetracycline Hydrochloride Capsules. Discontinue alcoholic beverage or other products containing propylene glycol during and for at least 3 days after therapy with Bismuth Subsalicylate Chewable Tablets/Metronidazole Tablets/Tetracycline Hydrochloride Capsules (see CONTRAINDICATIONS).

Oral Contraceptives

Concurrent use of Bismuth Subsalicylate Chewable Tablets/Metronidazole Tablets/Tetracycline Hydrochloride Capsules with oral contraceptive may make oral contraceptives less effective due to an interaction with the tetracycline component of Bismuth Subsalicylate Chewable Tablets/Metronidazole Tablets/Tetracycline Hydrochloride Capsules. Breakthrough bleeding has been reported. Women of child-bearing potential should use a different or additional form of contraception while taking Bismuth Subsalicylate Chewable Tablets/Metronidazole Tablets/Tetracycline Hydrochloride Capsules.

Anticoagulants

Bismuth Subsalicylate Chewable Tablets/Metronidazole Tablets/Tetracycline Hydrochloride Capsules may alter the anticoagulant effects of warfarin and other oral coumarin anticoagulants. Salicylates may cause an increased risk of bleeding when administered with anticoagulant therapy. Metronidazole has been reported to potentiate the anticoagulant effect of warfarin, and other oral coumarin anticoagulants, resulting in a prolongation of prothrombin time. Tetracycline has been shown to depress plasma prothrombin activity. Prothrombin time, International Normalized Ratio (INR), or other suitable anticoagulation tests should be closely monitored if Bismuth Subsalicylate Chewable Tablets/Metronidazole Tablets/Tetracycline Hydrochloride Capsules is administered concomitantly with warfarin. Patients should also be monitored for evidence of bleeding.

Lithium

In patients stabilized on relatively high doses of lithium, short-term use of Bismuth Subsalicylate Chewable Tablets/Metronidazole Tablets/Tetracycline Hydrochloride Capsules may cause elevation of serum lithium concentrations and signs of lithium toxicity due to the interaction between metronidazole and lithium. Serum lithium and serum creatinine concentrations should be monitored several days after beginning treatment with Bismuth Subsalicylate Chewable Tablets/Metronidazole Tablets/Tetracycline Hydrochloride Capsules to detect any increase that may precede clinical symptoms of lithium toxicity.

Antacids, Multivitamins, or Dairy Products

The absorption of Bismuth Subsalicylate Chewable Tablets/Metronidazole Tablets/Tetracycline Hydrochloride Capsules may be reduced if administered with antacids containing aluminium, calcium, or magnesium; preparations containing iron, zinc, or sodium bicarbonate; or milk or dairy products due to the interaction between these products and tetracycline. These products should not be consumed concomitantly with Bismuth Subsalicylate Chewable Tablets/Metronidazole Tablets/Tetracycline Hydrochloride Capsules. However, the clinical significance of reduced tetracycline systemic exposure is unknown as the relative contribution of systemic versus local antimicrobial activity against Helicobacter pylori has not been established.

Antidiabetic agents, Aspirin, Probenecid, or Sulfinpyrazone

Caution is advised in the administration of bismuth subsalicylate to patients taking medication for diabetes (possible enhanced hypoglycemic effect when given with salicylates) or patients taking aspirin (may increase the risk of salicylate toxicity), probenecid, or sulfinpyrazone (uricosuric effects of probenecid or sulfinpyrazone may be decreased) (see CONTRAINDICATIONS, WARNINGS).

Busulfan

Metronidazole has been reported to increase plasma concentrations of busulfan, which can result in an increased risk for serious busulfan toxicity. Bismuth Subsalicylate Chewable Tablets/Metronidazole Tablets/Tetracycline Hydrochloride Capsules should not be administered concomitantly with busulfan unless the benefit outweighs the risk. If no therapeutic alternatives to Bismuth Subsalicylate Chewable Tablets/Metronidazole Tablets/Tetracycline Hydrochloride Capsules are available, and concomitant administration with busulfan is medically needed, frequent monitoring of busulfan plasma concentration should be performed and the busulfan dose should be adjusted accordingly.

Inhibitors of CYP450 liver enzymes

The simultaneous administration of Bismuth Subsalicylate Chewable Tablets/Metronidazole Tablets/Tetracycline Hydrochloride Capsules and drugs that inhibit microsomal liver enzymes, such as cimetidine, may result in a prolonged half-life and decreased plasma clearance of metronidazole.

Inducers of CYP450 liver enzymes

The simultaneous administration of Bismuth Subsalicylate Chewable Tablets/Metronidazole Tablets/Tetracycline Hydrochloride Capsules and drugs that induce microsomal liver enzymes, such as phenytoin or phenobarbital, may accelerate the elimination of metronidazole, resulting in reduced plasma concentrations of metronidazole. Impaired clearance of phenytoin has also been reported in this situation. Monitor phenytoin concentrations during treatment with Bismuth Subsalicylate Chewable Tablets/Metronidazole Tablets/Tetracycline Hydrochloride Capsules.

Carcinogenesis, Mutagenesis, Impairment of Fertility:

No long-term studies have been performed to evaluate the effect of Bismuth Subsalicylate Chewable Tablets/Metronidazole Tablets/Tetracycline Hydrochloride Capsules on carcinogenesis, mutagenesis, or impairment of fertility.

Bismuth subsalicylate
No long-term toxicity studies have been conducted with bismuth subsalicylate. Bismuth did not show mutagenic potential in the NTP salmonella plate assay. No reproductive toxicity studies have been conducted with bismuth subsalicylate.

Metronidazole
Metronidazole has shown evidence of carcinogenic activity in a number of studies involving chronic, oral administration in mice and rats. Prominent among the effects in the mouse was an increased incidence of pulmonary tumorigenesis. This has been observed in all six reported studies in that species, including one study in which the animals were dosed on an intermittent schedule (administration during every fourth week only). At the highest dose levels, (approximately 500 mg/kg/day, which is approximately 1.6 times the indicated human dose for a 60 kg adult based on body surface area) there was a statistically significant increase in the incidence of malignant liver tumors in male mice. Also, the published results of one of the mouse studies indicate an increase in the incidence of malignant lymphomas as well as pulmonary neoplasms associated with lifetime feeding of the drug. All these effects are statistically significant. Long-term, oral-dosing studies in the rat showed statistically significant increases in the incidence of various neoplasms, particularly in mammary and hepatic tumors, among female rats administered metronidazole over those noted in the concurrent female control groups. Two lifetime tumorigenicity studies in hamsters have been performed and reported to be negative. Although metronidazole has shown mutagenic activity in a number of in vitro assay systems, studies in mammals (in vivo) have failed to demonstrate a potential for genetic damage.

Fertility studies have been conducted with male rats and mice with divergent results. Metronidazole, at doses up to 400 mg/kg/day (approximately 3 times the indicated human dose based on mg/m^2) for 28 days, failed to produce any adverse effects on fertility and testicular function in male rats. In another study where rats were treated with up to 400 mg/kg/day for 8 weeks, there was severe degeneration of the seminiferous epithelium in the testes which was associated with a marked decrease in testicular spermatid counts and epididymal sperm counts and a marked decrease in fecundity. These effects were partially reversible.

Fertility studies have been performed in male mice at doses up to six times the maximum recommended human dose based upon mg/m^2 and have revealed no evidence of impaired fertility. Another fertility study was performed in male mice at oral doses of 500 mg/kg/day (approximately 2 times the indicated human dose based on mg/m²) for 14 days. Metronidazole significantly decreased testes and epididymides weight, decreased sperm viability, and increased the incidence of abnormal sperm. The viability of sperm was normal by 2 months after the start of the treatment.

Tumors affecting the liver, lungs, mammary, and lymphatic tissues have been detected in several studies of metronidazole in rats and mice, but not hamsters.

Pulmonary tumors have been observed in all six reported studies in the mouse, including one study in which the animals were dosed on an intermittent schedule (administration during every fourth week only). Malignant liver tumors were increased in male mice treated at approximately 1500 mg/m^2 (similar to the maximum recommended daily dose, based on body surface area comparisons). Malignant lymphomas and pulmonary neoplasms were also increased with lifetime feeding of the drug to mice. Mammary and hepatic tumors were increased among female rats administered oral metronidazole compared to concurrent controls. Two lifetime tumorigenicity studies in hamsters have been performed and reported to be negative.

Metronidazole has shown mutagenic activity in in vitro assay systems including the Ames test. Studies in mammals in vivo have failed to demonstrate a potential for genetic damage.

Metronidazole failed to produce any adverse effects on fertility or testicular function in male rats at doses up at 400 mg/kg/day (similar to the maximum recommended clinical dose, based on body surface area comparisons) for 28 days. However, rats treated at the same dose for 6 weeks or longer were infertile and showed severe degeneration of the seminiferous epithelium in the testes as well as marked decreases in testicular spermatid counts and epididymal sperm counts. Fertility was restored in most rats after an eight week, drug-free recovery period.

Tetracycline hydrochloride
There has been no evidence of carcinogenicity for tetracycline hydrochloride in studies conducted with rats and mice. Some related antibiotics (oxytetracycline, minocycline) have shown evidence of oncogenic activity in rats.

There was evidence of mutagenicity by tetracycline hydrochloride in two in vitro mammalian cell assay systems (L51784y mouse lymphoma and Chinese hamster lung cells).

Tetracycline hydrochloride had no effect on fertility when administered in the diet to male and female rats at a daily intake of 25 times the human dose.

Pregnancy

Pregnancy Category D
Bismuth Subsalicylate Chewable Tablets/Metronidazole Tablets/Tetracycline Hydrochloride Capsules contains bismuth subsalicylate, metronidazole, and tetracycline hydrochloride. There are no adequate and well-controlled studies of Bismuth Subsalicylate Chewable Tablets/Metronidazole Tablets/Tetracycline Hydrochloride Capsules in pregnant women. However, tetracycline can cause fetal harm when administered to a pregnant woman. The use of tetracycline during the second and third trimester of pregnancy can also cause permanent discoloration of the teeth (yellow-gray brown) and possibly inhibit bone development. Administration of oral tetracycline to pregnant rats at various doses resulted in yellow fluorescence in teeth and bones in the newborn animals. If this drug is used during pregnancy, or if the patient becomes pregnant while taking this drug, the patient should be apprised of the potential hazard to the fetus (see WARNINGS).

The available human and animal data are summarized below for each of Bismuth Subsalicylate Chewable Tablets/Metronidazole Tablets/Tetracycline Hydrochloride Capsules active ingredients:

Tetracycline
Published case reports have described the yellowing of bones and teeth in human infants exposed to tetracycline during the second and third trimester of pregnancy. The yellowing is caused by the direct deposition of tetracycline during the mineralization process. This discoloration is more common during long-term use of the drug but has also been observed following repeated short-term courses. All tetracyclines form a stable calcium complex in any bone forming tissue. A decrease in fibula growth rate was observed in premature infants given oral tetracycline in doses of 25 mg/kg every six hours. This effect resolved when the drug was discontinued. One long-term follow-up study in children exposed to tetracycline in-utero showed no adverse effects on bone growth and development.

Tetracycline administered during pregnancy at high doses (greater than 2 g IV) was associated with rare but serious cases of maternal hepatotoxicity. This syndrome may result in stillborn or premature birth due to maternal pathology (see WARNINGS).

Results of animal studies indicate that tetracycline crosses the placenta, is found in fetal tissues, and can have toxic effects on the developing fetus (often related to reversible retardation of skeletal development). Evidence of embryotoxicity has also been noted in animals treated early in pregnancy. Multiple studies of limited design were conducted with pregnant and lactating female rats that resulted in fetuses and neonates with yellow discoloration of bones and teeth.

Metronidazole
There are published data from case-control studies, cohort studies, and 2 meta-analyses that include more than 5000 pregnant women who used metronidazole during pregnancy. Many studies included first trimester exposures. One study showed an increased risk of cleft lip, with or without cleft palate, in infants exposed to metronidazole in-utero; however, these findings were not confirmed. In addition, more than ten randomized, placebo-controlled clinical trials enrolled more than 5000 pregnant women to assess the use of antibiotic treatment (including metronidazole) for bacterial vaginosis on the incidence of preterm delivery. Most studies did not show an increased risk for congenital anomalies or other adverse fetal outcomes following metronidazole exposure during pregnancy. Three studies conducted to assess the risk of infant cancer following metronidazole exposure during pregnancy did not show an increased risk; however, the ability of these studies to detect such a signal was limited.

Metronidazole crosses the placental barrier and its effects on the human fetal organogenesis are not known. No fetotoxicity was observed when metronidazole was administered orally to pregnant mice at 10 mg/kg/day, approximately 5 percent of the indicated human dose (1500 mg/day) based on body surface area; however in a single small study where the drug was administered intraperitoneally, some intrauterine deaths were observed. The relationship of these findings to the drug is unknown.

Bismuth subsalicylate

Animal reproductive studies have not been conducted with bismuth subsalicylate. It is also not known whether bismuth subsalicylate can cause fetal harm when administered to a pregnant woman or can affect reproduction capacity.

Labor and Delivery: The effect of this therapy on labor and delivery is unknown.

Nursing Mothers: Bismuth Subsalicylate Chewable Tablets/Metronidazole Tablets/Tetracycline Hydrochloride Capsules contains bismuth subsalicylate, metronidazole, and tetracycline hydrochloride. Metronidazole is present in human milk at concentrations similar to maternal serum levels, and infant serum levels can be close to or comparable to infant therapeutic levels. Because of the potential for tumorigenicity shown for metronidazole in animal studies, a decision should be made whether to discontinue nursing or to discontinue metronidazole, taking into account the importance of the therapy to the mother. Alternatively, a nursing mother may choose to pump and discard human milk for the duration of Bismuth Subsalicylate Chewable Tablets/Metronidazole Tablets/Tetracycline Hydrochloride Capsules, and for 24 hours after therapy ends and feed her infant stored human milk or formula.

Tetracycline is present in human milk at concentrations similar to maternal serum levels; however, it binds with calcium in human milk. Data indicate that oral absorption of tetracycline in infants is low due to the calcium binding in human milk. It is not known whether bismuth subsalicyate is excreted in human milk.

Pediatric Use: Safety and effectiveness of Bismuth Subsalicylate Chewable Tablets/Metronidazole Tablets/Tetracycline Hydrochloride Capsules in pediatric patients infected with H. pylori have not been established.

Tetracycline use in children may cause permanent discoloration of the teeth. Enamel hypoplasia has also been reported. Bismuth Subsalicylate Chewable Tablets/Metronidazole Tablets/Tetracycline Hydrochloride Capsules should not be used in children up to 8 years of age (see WARNINGS).

Geriatric Use: Clinical studies of Bismuth Subsalicylate Chewable Tablets/Metronidazole Tablets/Tetracycline Hydrochloride Capsules did not include sufficient numbers of subjects aged 65 and over to determine whether they respond differently from younger subjects. Other reported clinical experience has not identified differences in responses between the elderly and younger patients. In general, elderly patients may have a greater frequency of decreased hepatic, renal, or cardiac function, and concomitant diseases or other drug therapies. Bismuth subsalicylate, a component of Bismuth Subsalicylate Chewable Tablets/Metronidazole Tablets/Tetracycline Hydrochloride Capsules, is known to be substantially excreted by the kidney, and the risk of adverse reactions may be greater in patients with impaired renal function. Because elderly patients are more likely to have decreased renal function, additional monitoring may be required (see CONTRAINDICATIONS).

Renal Impairment: The antianabolic action of the tetracyclines may cause an increase in blood urea nitrogen (BUN). While this is not a problem in those with normal renal function, in patients with significantly impaired renal function, higher serum levels of tetracycline may lead to azotemia, hyperphosphatemia, and acidosis (see CONTRAINDICATIONS).

Hepatic Impairment: Patients with severe hepatic disease metabolize metronidazole slowly, with resultant accumulation of metronidazole and its metabolites in plasma. Use Bismuth Subsalicylate Chewable Tablets/Metronidazole Tablets/Tetracycline Hydrochloride Capsules with caution in patients with hepatic impairment (see PRECAUTIONS).

ADVERSE REACTIONS:

Clinical Trials Experience

Because clinical trials are conducted under widely varying conditions, adverse reaction rates observed in the clinical trials of a drug cannot be directly compared to rates in the clinical trials of another drug and may not reflect the rates observed in practice.

The most common adverse reactions (≥ 1%) reported in clinical trials when all three components of this therapy were given concomitantly are listed in Table 1 below. The majority of the adverse reactions were related to the gastrointestinal tract, were reversible, and infrequently led to discontinuation of therapy.

Table 1: Incidence of Adverse Reactions Reported in Clinical Trials (≥ 1%)†
 | Bismuth Subsalicylate, Metronidazole, and Tetracycline ‡ (N = 266)
Adverse Reactions | % Patients
Nausea | 12.0
Diarrhea | 6.8
Abdominal Pain | 6.8
Melena | 3.0
Upper Respiratory Infection | 2.3
Constipation | 1.9
Anorexia | 1.5
Asthenia | 1.5
Vomiting | 1.5
Discolored Tongue* | 1.5
Headache | 1.5
Dyspepsia | 1.5
Dizziness | 1.5
Stool Abnormality** | 1.1
Duodenal Ulcer | 1.1
Sinusitis | 1.1
Taste Perversion*** | 1.1
Flatulence | 1.1
GI Hemorrhage | 1.1
Pain | 1.1
Insomnia | 1.1
Anal Discomfort | 1.1
Paresthesia | 1.1

* darkening of the tongue
** black or dark stools
*** metallic taste
† Includes reactions reported at ≥1% in patients taking bismuth subsalicylate, metronidazole, and tetracycline in Studies 1, 2, 3, and 4 (see CLINICAL STUDIES).
‡ In Studies 1, 2, and 3(N = 197), most patients were on concomitant acid suppression therapy.

The additional adverse reactions (< 1%) reported in clinical trials when all three components of this therapy were given concomitantly are listed below and divided by body system:

Gastrointestinal: dry mouth, dysphagia, eructation, GI monilia, glossitis, intestinal obstruction, rectal hemorrhage, stomatitis

Skin: acne, ecchymosis, photosensitivity reaction (see PRECAUTIONS), pruritus, rash

Cardiovascular: cerebral ischemia, chest pain, hypertension, myocardial infarction

CNS: nervousness, somnolence

Musculoskeletal: arthritis, rheumatoid arthritis, tendonitis

Metabolic: SGOT increase, SGPT increase

Urogenital: urinary tract infection

Other: conjunctivitis, flu syndrome, infection, malaise, neoplasm, rhinitis, syncope, tooth disorder

Other Important Adverse Reactions from Labeling for the Individual Components of Bismuth Subsalicylate Chewable Tablets/Metronidazole Tablets/Tetracycline Hydrochloride Capsules

Metronidazole

Blood and Lymphatic system disorders: Reversible neutropenia (leucopenia) in cases of prolonged treatment; rarely reversible thrombocytopenia however no persistent hematological abnormalities attributable to metronidazole have been observed (see PRECAUTIONS).

Cardiac disorders: Flattening of the T-wave may be seen in electrocardiographic tracings.

Gastrointestinal disorders: Nausea, vomiting, diarrhea, abdominal pain, constipation, anorexia, metallic taste, furry tongue, glossitis, stomatitis and candida overgrowth (see PRECAUTIONS).

Hypersensitivity/Immune system disorders: Urticaria, erythematous rash, Stevens-Johnson syndrome, toxic epidermal necrolysis, flushing, nasal congestion, dryness of the mouth (or vagina or vulva), and fever (see CONTRAINDICATIONS).

Metabolism and nutrition disorders: Pancreatitis.

Nervous system disorders: Convulsive seizures, encephalopathy, aseptic meningitis, optic and peripheral neuropathy, headache, syncope, dizziness, vertigo, incoordination, ataxia, confusion, dysarthria, irritability, depression, weakness, and insomnia (see WARNINGS).

Dermatologic disorders: Erythematous rash and pruritus.

Renal and urinary disorders: Dysuria, cystitis, polyuria, incontinence, darkened urine, and a sense of pelvic pressure.

Other: Dyspareunia, decrease of libido, proctitis, joint pains.

Tetracycline Hydrochloride

Blood and lymphatic system disorders: Hemolytic anemia, thrombocytopenia, thrombocytopenic purpura, neutropenia, and eosinophilia.

Gastrointestinal disorders: Nausea, vomiting, diarrhea, anorexia, glossitis, black hairy tongue, dysphagia, enterocolitis, inflammatory lesions (with Candida overgrowth) in the anogenital region, esophagitis and esophageal ulceration.

Nervous system disorders: Intracranial hypertension including pseudotumor cerebri, tinnitus, and myasthenic syndrome.

Renal and urinary disorders: Increased BUN.

Skin and subcutaneous tissue disorders: Maculopapular and erythematous rashes, DRESS syndrome (drug rash with eosinophilia and systemic symptoms), Steven-Johnson syndrome, toxic epidermal necrolysis, erythema multiforme, onycholysis, discoloration of the nails, exfoliative dermatitis and photosensitivity have been rarely reported (see WARNINGS).

Liver: Hepatotoxicity and liver failure.

Hypersensitivity reactions: Urticaria, angioedema, anaphylaxis, Henoch-Schonlein purpura, pericarditis, exacerbation of systemic lupus erythematosus, and serum sickness-like reactions.

OVERDOSAGE:

In case of an overdose, patients should contact a physician, poison control center, or emergency room.

Bismuth Subsalicylate: The main concern of an acute bismuth subsalicylate (BSS) overdose focuses on the salicylate burden and not on bismuth, since less than 1% of the bismuth is normally absorbed. Each 262.4-mg tablet of BSS contains an amount of salicylate comparable to approximately 130 mg aspirin. Acute ingestion of less than 150 mg/kg of aspirin (i.e., less than one tablet of bismuth subsalicylate per kilogram of body weight) is not expected to lead to toxicity. Mild to moderate toxicity may result from the ingestion of 150 to 300 mg/kg, while severe toxicity may occur from ingestions over 300 mg/kg. Salicylate intoxication presents a complex clinical picture. Multiple respiratory and metabolic effects result in fluid, electrolyte, glucose, and acid-base disturbances. Initial symptoms of salicylate toxicity include hyperpnea, nausea, vomiting, tinnitus, hyperpyrexia, lethargy, tachycardia, and confusion. In severe cases, these symptoms may progress to severe hyperpnea, convulsions, pulmonary or cerebral edema, respiratory failure, cardiovascular collapse, coma, and death.

Treatment: There is no specific antidote for salicylate poisoning. If there are no contraindications, vomiting should be induced as soon as possible with syrup of ipecac, or gastric lavage should be instituted, provided that no more than one hour has elapsed since ingestion. Activated charcoal and a cathartic may be administered as primary decontamination therapy in those cases where greater than one hour has elapsed since ingestion, or to further decontaminate the gastrointestinal tract in those who have already received ipecac or gastric lavage. Plasma salicylate levels may be useful; a common nomogram can be used to help predict the severity of intoxication. Supportive and symptomatic treatment should be provided, with emphasis on correcting fluid, electrolyte, blood glucose, and acid-base disturbances. Elimination may be enhanced by urinary alkalinization, hemodialysis, or hemoperfusion. Since hemodialysis aids in correcting acid-base disturbances, this method may be preferred over hemoperfusion.

Metronidazole: Symptoms of metronidazole toxicity include nausea, vomiting, and neurotoxic effects such as ataxia, seizures and peripheral neuropathy.

Treatment: There is no specific antidote for metronidazole overdose. Management of the patient should consist of symptomatic and supportive therapy. Metronidazole is dialyzable.

Tetracycline: Therapeutic and overdose quantities of tetracycline can cause gastrointestinal symptoms such as nausea, vomiting, and diarrhea.

Treatment: There is no specific antidote for tetracycline overdose. Management of the patient should consist of symptomatic and supportive therapy. Tetracycline is not dialyzable.

DOSAGE AND ADMINISTRATION:

Adults: The recommended dosages are: bismuth subsalicylate, 525 mg (two 262.4 mg-chewable tablets), metronidazole, 250 mg (one 250-mg tablet), and tetracycline hydrochloride, 500 mg (one 500-mg capsule) taken four times daily for 14 days plus an H^2 antagonist approved for the treatment of acute duodenal ulcer. Patients should be instructed to take the medicines at mealtimes and at bedtime. The bismuth subsalicylate tablets should be chewed and swallowed. The metronidazole tablet and tetracycline hydrochloride capsule should be swallowed whole with a full glass of water (8 ounces). Concomitantly prescribed H^2 antagonist therapy should be taken as directed.

Ingestion of adequate amounts of fluid, particularly with the bedtime dose of tetracycline hydrochloride, is recommended to reduce the risk of esophageal irritation and ulceration (see ADVERSE REACTIONS).

Missed doses can be made up by continuing the normal dosing schedule until the medication is gone. Patients should not take double doses. If more than 4 doses are missed, the prescriber should be contacted.

HOW SUPPLIED:

Bismuth Subsalicylate Chewable Tablets/Metronidazole Tablets/Tetracycline Hydrochloride Capsules is supplied in a carton containing patient instructions, patient reminders, and 14 blister cards, each card containing the following daily dosage:

8 bismuth subsalicylate 262.4-mg chewable tablets, each pink round tablet debossed “W10”.

4 metronidazole 250-mg tablets are round, white, debossed with “WPI” on one side and “3969” on the other.

4 tetracycline hydrochloride 500-mg capsules, each black/yellow capsule imprinted with “WPI” on cap and “2235” on the body.

NDC 70556-103-14 carton containing 14 days of therapy
Store at 20° to 25° C (68° to 77° F). [See USP Controlled Room Temperature.].

CLINICAL STUDIES:

Eradication of H. pylori in Patients with Active Duodenal Ulcer Disease: Three clinical trials in the U.S. (Studies 1, 2 and 3) evaluated the effect of therapy on the eradication of H. pylori using bismuth subsalicylate, metronidazole, and tetracycline hydrochloride. The patient population in these studies consisted predominantly of duodenal ulcer patients with active disease. In addition to bismuth subsalicylate, metronidazole, tetracycline hydrochloride triple therapy, most patients were also prescribed antisecretory therapy at doses recommended for ulcer healing, with the majority receiving ranitidine. The efficacy in these studies was assessed using H. pylori eradication, or cure of infection. Use of cure of infection as a surrogate for reduced ulcer recurrence is based on an extensive review of the literature. Eradication rates are derived from results of Studies 1 (randomized, controlled study) and Study 3 (uncontrolled, nonrandomized) and are shown in Table 2. H. pylori eradication was defined as no positive test (culture, histology, rapid urease, or 13C breath test) at least 4 weeks following the end of treatment. In the analysis performed, dropouts and patients with missing H. pylori tests post-treatment were excluded. Bismuth Subsalicylate Chewable Tablets/Metronidazole Tablets/Tetracycline Hydrochloride Capsules (bismuth subsalicylate, metronidazole, and tetracycline hydrochloride) was effective in eradicating H. pylori.

Table 2: H. pylori Eradication Rates in Patients with Active Duodenal Ulcer Disease (Studies 1 and 3)
Study Number | Eradication Rate in Duodenal Ulcer Patients† | 95% Confidence Intervals
Study 1 | 77% (N = 39) | 61% - 89%
Study 3 | 82% (N = 51) | 70% - 92%

† Evaluable patients were defined as having a confirmed duodenal ulcer within 2 years prior to treatment and having taken 14 days of bismuth subsalicylate, metronidazole, and tetracycline (range 11 to 17 days). Eradication was defined as no evidence of H. pylori infection by culture, histology, rapid urease test and/or urea breath test from at least 4 weeks post-treatment up to 1 year posttreatment.

Study 2 evaluated the long-term outcome in patients treated for active duodenal ulcer by frequently monitoring for ulcer recurrence for up to 1 year after therapy. This study compared patients who received bismuth subsalicylate (BSS), metronidazole (MTZ), and tetracycline hydrochloride (TCN) for 2 weeks with ranitidine to those who received ranitidine alone. The ulcer recurrence rates at 6 months (Table 3) and one year (Table 4) regardless of post-treatment eradication status are summarized below for duodenal ulcer patients who were H. pylori positive at baseline.

Table 3: Duodenal Ulcer Recurrence Rates at 6 Months†
Therapy | All Patients | H. pylori Negative Patients Post-Treatment
BSS/MTZ/TCN + Ranitidine | 4% (1/25) | 6% (1/18)
Ranitidine | 85% (17/20) | 100% (1/1)

Table 4: Duodenal Ulcer Recurrence Rates at 12 Months†
Therapy | All Patients | H. pylori Negative Patients Post-Treatment
BSS/MTZ/TCN + Ranitidine | 9% (2/2) | 13% (2/16)
Ranitidine | 95% (18/19) | 100% (1/1)

† Includes all patients randomized to therapy who were H. pylori positive at baseline (by culture, histology, and/or urea breath test) who had ulcer healing and 24 or 48 weeks of endoscopic follow-up data.

Eradication of H. pylori in Patients with a History of Duodenal Ulcer Disease: A controlled, multicenter trial (Study 4) in the U.S. compared the rates of eradication of H. pylori following 14 days of treatment with Bismuth Subsalicylate Chewable Tablets/Metronidazole Tablets/Tetracycline Hydrochloride Capsules (bismuth subsalicylate, metronidazole, and tetracycline hydrochloride) or control (bismuth subsalicylate, metronidazole placebo, and tetracycline placebo) in 103 patients infected with H. pylori who had a history of duodenal ulcer disease. No H2-receptor antagonist was used. H. pylori eradication was assessed by rapid urease testing, histology, and culture at least 4 weeks after the last dose. Bismuth Subsalicylate Chewable Tablets/Metronidazole Tablets/Tetracycline Hydrochloride Capsules was effective in eradicating H. pylori. The eradication rates are noted in the table below:

Table 5: H. pylori Eradication Rates in Patients with a History of Duodenal Ulcer Disease (Study 4)
Population | Evaluable Population† |  | Intent-To-Treat Population‡
Therapy | Bismuth Subsalicylate Chewable Tablets/Metronidazole Tablets/Tetracycline Hydrochloride Capsules | Control | Bismuth Subsalicylate Chewable Tablets/Metronidazole Tablets/Tetracycline Hydrochloride Capsules | Control
Eradication Rate (Number of Patients) | 71% (40/56) | 7% (2/30) | 72% (41/57) | 6% (2/32)
95% confidence interval | 60, 83 | 0a, 16 | 60, 84 | 0a, 15

a The lower limit for this calculation was -2.2 but was truncated to 0 for reporting purposes.

† Evaluable patients were defined as having a history of a confirmed duodenal ulcer prior to treatment and having taken ≥ 70% of each component of Bismuth Subsalicylate Chewable Tablets/Metronidazole Tablets/Tetracycline Hydrochloride Capsules (bismuth subsalicylate, metronidazole, tetracycline hydrochloride) during the 14-day dosing period. Eradication was defined as no evidence of H. pylori infection by two or three diagnostic tests (culture, histology, and rapid urease test) from at least 4 weeks to 6 weeks post-treatment. Excluded from the evaluable population were patients who were noncompliant with medication, patients who were not infected with H. pylori at baseline, and patients without ulcer documentation. Three patients in the Bismuth Subsalicylate Chewable Tablets/ Metronidazole Tablets/Tetracycline Hydrochloride Capsules group and one patient in the Control group were included as eradication failures because they withdrew from the study due to treatment-related adverse events.

‡ Patients were included in the analysis if they had documented H. pylori infection at baseline and had confirmed duodenal ulcer disease. All dropouts were included as failures of therapy. Eradication was defined as no evidence of H. pylori infection by culture, histology, or rapid urease test.

Compliance with the triple therapy regimen was also evaluated in the clinical study. In the intent-to-treat population, 93% of Bismuth Subsalicylate Chewable Tablets/ Metronidazole Tablets/Tetracycline Hydrochloride Capsules group took at least 75% of their medication.

PEPTO-BISMOL is the registered trademark of The Procter & Gamble Company.

Bismuth Subsalicylate Chewable Tablets, 262.4 mg are manufactured by:
WES Pharma Inc
Westminster, MD 21157 USA

Metronidazole Tablets USP, 250 mg are manufactured by:
Watson Pharma Private Limited
Verna, Salcette Goa 403 722 INDIA

Tetracycline Hydrochloride Capsules USP, 500 mg are manufactured by:
Watson Pharma Private Limited
Verna, Salcette Goa 403 722 INDIA

for:
Ailex Pharmaceuticals, LLC
Lenexa, KS 66219 USA

Rev.: 08/2018

PHARMACIST INFORMATION AND COUNSELING AID

Bismuth Subsalicylate Chewable Tablets, 262.4 mg
Metronidazole Tablets USP, 250 mg
Tetracycline Hydrochloride Capsules USP, 500 mg
(Bismuth Subsalicylate Chewable Tablets/Metronidazole Tablets/Tetracycline Hydrochloride Capsules)

To reduce the development of drug-resistant bacteria and maintain the effectiveness of Bismuth Subsalicylate Chewable Tablets/Metronidazole Tablets/Tetracycline Hydrochloride Capsules and other antibacterial drugs, Bismuth Subsalicylate Chewable Tablets/Metronidazole Tablets/Tetracycline Hydrochloride Capsules should be used only to treat or prevent infections that are proven or strongly suspected to be caused by bacteria.

Ailex Pharmaceuticals, LLC

PHARMACIST INFORMATION AND COUNSELING AID

Not intended for distribution to Patient

• This Counseling Aid contains concise information for the Pharmacist and is meant to aid in counseling; please refer to the attached Package Insert for complete prescribing information.
• There is a detailed PATIENT INFORMATION BOOKLET contained in this package which should be read by the patient prior to initiating therapy.
• Instructions for opening the enclosed dosing blister cards can be found on the top of this package.

Bismuth Subsalicylate Chewable Tablets, 262.4 mg
Metronidazole Tablets USP, 250 mg
Tetracycline Hydrochloride Capsules USP, 500 mg
(Bismuth Subsalicylate Chewable Tablets/Metronidazole Tablets/Tetracycline Hydrochloride Capsules)

1. What is the most important information my patient should know about Bismuth Subsalicylate Chewable Tablets/Metronidazole Tablets/Tetracycline Hydrochloride Capsules?
a. Scientists have discovered that most ulcers are caused by an infection from a specific germ called H. pylori. Helicobacter pylori (H. pylori) infection has been found to play a primary role in the pathogenesis of duodenal ulcers, and is considered the causative organism in 80% to 95% of patients with duodenal ulcers.
b. Each pill of every dose is important. Studies have shown that taking all this medicine is very important to eradicate all the ulcer-causing germs. If doses are skipped or treatment is stopped early, some of these germs may not be eradicated and another ulcer can develop.

2. What is Bismuth Subsalicylate Chewable Tablets/Metronidazole Tablets/Tetracycline Hydrochloride Capsules?
a. The components of Bismuth Subsalicylate Chewable Tablets/Metronidazole Tablets/Tetracycline Hydrochloride Capsules (bismuth subsalicylate, metronidazole, and tetracycline hydrochloride) are indicated for the treatment of patients with an active duodenal ulcer associated with H. pylori infection. The eradication of H. pylori has been demonstrated to reduce the risk of duodenal ulcer recurrence. Appropriate doses of an H2 antagonist indicated for the treatment of active duodenal ulcer should be prescribed for ulcer healing.
b. Bismuth Subsalicylate Chewable Tablets/Metronidazole Tablets/Tetracycline Hydrochloride Capsules is a combination of three antimicrobial agents: bismuth subsalicylate, metronidazole, and tetracycline hydrochloride. Clinical trials using this combination have demonstrated H. pylori eradication in up to 82% of patients with a duodenal ulcer. Please note: bismuth subsalicylate is used in this combination for its antimicrobial properties and not for symptomatic relief of upset stomach.
c. Clinical data show that eradication of H. pylori is directly related to compliance. This therapy has been designed to enhance compliance and contains 14 blister cards, one for each day of the 14-day treatment plan, with each card divided into the 4 daily doses. The therapy also contains a patient-oriented information booklet and patient reminders.

3. Who should not take Bismuth Subsalicylate Chewable Tablets/Metronidazole Tablets/Tetracycline Hydrochloride Capsules?
Bismuth Subsalicylate Chewable Tablets/Metronidazole Tablets/Tetracycline Hydrochloride Capsules is contraindicated in the following patient populations:
a. Pregnant women. Advise pregnant women that Bismuth Subsalicylate Chewable Tablets/Metronidazole Tablets/Tetracycline Hydrochloride Capsules can cause fetal harm due to the tetracycline it contains. Tetracycline use during the second and third trimesters of pregnancy can cause permanent discoloration of the teeth (yellow-gray brown) and may inhibit bone development.
b. Nursing women. Advise women to avoid feeding their infants with their milk during Bismuth Subsalicylate Chewable Tablets/Metronidazole Tablets/Tetracycline Hydrochloride Capsules therapy. Women should either discontinue feeding or pump and discard their milk during treatment and for 24 hours after the last dose.
c. Pediatric patients.
d. Patients with renal or hepatic impairment.
e. Patients with known hypersensitivity to bismuth subsalicylate, metronidazole or other nitroimidazole derivatives, or any of the tetracyclines; this product does not contain aspirin, but should not be administered to those patients who have a known allergy to aspirin or salicylates.
f. Patients with evidence of, or a history of, blood dyscrasias.
g. Administer with caution in patients with central nervous system diseases.
h. Administer with caution in elderly patients who may suffer from asymptomatic renal and hepatic dysfunction.

4. How should my patient take Bismuth Subsalicylate Chewable Tablets/Metronidazole Tablets/Tetracycline Hydrochloride Capsules?
The medicines in this therapy have been demonstrated to treat the infection in the majority of cases when taken correctly. Treating the infection is important to reduce the risk of the ulcer coming back. (It may be useful to open the therapy and explain dosing while showing the patient one of the dosing blister cards.) Patients should be told that although it is common to feel better early in the course of therapy, the medication should be taken exactly as directed. Skipping doses or not completing the full course of therapy may (1) decrease the effectiveness of the immediate treatment and (2) increase the likelihood that bacteria will develop resistance and will not be treatable by Bismuth Subsalicylate Chewable Tablets/Metronidazole Tablets/Tetracycline Hydrochloride Capsules or other antibacterial drugs in the future.
a. Dosing:
i. Each dose includes 4 pills: 2 pink round chewable tablets (bismuth subsalicylate), 1 white round tablet (metronidazole), and 1 black and yellow capsule (tetracycline hydrochloride).
ii. Take 1 dose (all 4 pills) 4 times a day – at mealtimes and bedtime.
iii. Chew and swallow the 2 pink tablets.
iv. Then swallow the white tablet and black and yellow capsule whole with a full glass of water (8 ounces).
v. Remember: Chew-Chew-Swallow-Swallow = 1 dose.
vi. All 4 daily doses are contained on an individual blister card.
vii. This therapy contains 14 blister cards, one card for each day of the 14day treatment plan.
viii. If you miss a dose, do not take a double dose. Instead, make up any missed doses by continuing your normal dosing schedule until the medication is gone. (Please contact prescriber if more than 4 doses are missed.)
ix. Each dose should be taken with a full glass of water (8 ounces), especially the bedtime dose (to reduce risk of esophageal irritation and ulceration due to tetracycline).
x. Concomitantly prescribed H2 antagonist therapy should be taken as directed.
b. In case of an overdose, patients should contact a physician, poison control center, or emergency room.

5. What should my patients avoid while taking Bismuth Subsalicylate Chewable Tablets/Metronidazole Tablets/Tetracycline Hydrochloride Capsules?
Patients should avoid:
a. Methoxyflurane (an anaesthesia). Concurrent use of tetracycline and methoxyflurane has been reported to result in fatal renal toxicity.
b. Disulfiram (treatment for alcoholism) within the last 2 weeks. Psychotic episodes have been reported in patients using metronidazole and disulfiram concurrently.
c. Alcohol. There is a potential for a disulfiram-like interaction with metronidazole. Patients should be warned not to drink alcohol or products containing propylene glycol during therapy and for at least 3 days after completion of all doses due to potential metronidazole effects.
d. Antacids containing aluminum, calcium, or magnesium; preparations containing iron, zinc, or sodium bicarbonate; and milk or dairy products. Absorption of tetracycline may be impaired when co-administered.
e. The sun (or sunlamps) because of possible photosensitivity due to tetracycline.
f. Other medications without first consulting with your pharmacist or prescriber.

6. The administration of any of the following drugs with Bismuth Subsalicylate Chewable Tablets/Metronidazole Tablets/Tetracycline Hydrochloride Capsules may result in adverse reactions or insufficient drug efficacies:
a. Oral contraceptives. As with many antibacterial preparations, concomitant use of Bismuth Subsalicylate Chewable Tablets/Metronidazole Tablets/Tetracycline Hydrochloride Capsules may reduce the effectiveness of estrogen-containing oral contraceptives; breakthrough bleeding may occur. Patients should be advised to use an additional or different form of contraception. Women who become pregnant while taking Bismuth Subsalicylate Chewable Tablets/Metronidazole Tablets/Tetracycline Hydrochloride Capsules should be advised to notify their prescriber immediately.
b. Anticoagulants. Individual components of Bismuth Subsalicylate Chewable Tablets/Metronidazole Tablets/Tetracycline Hydrochloride Capsules have the potential to interact with anticoagulants. Monitoring anticoagulant therapy with appropriate adjustment of the anticoagulant dosage may be warranted if concurrent therapy is instituted. (See Package Insert.)
c. Lithium. In patients stabilized on relatively high doses of lithium, short-term metronidazole therapy has been associated with elevation of serum lithium and, in a few cases, signs of lithium toxicity. Serum lithium and serum creatinine should be obtained several days after beginning metronidazole to detect any increase that may precede clinical symptoms of lithium toxicity.
d. Antidiabetic agents. There is a possible enhanced hypoglycemic effect when given with salicylates.
e. Cimetidine. The simultaneous administration of drugs that decrease microsomal liver enzyme activity, such as cimetidine, may prolong the half-life and decrease plasma clearance of metronidazole.
f. Others. See the Package Insert regarding the following possible, suspected, or confirmed interactions: aspirin, probenecid, sulfinpyrazone, methoxyflurane, disulfiram (within 2 weeks), lithium, microsomal liver enzyme inducers, such as phenytoin or phenobarbital, and microsomal liver enzyme inhibitors.
g. Although there is an anticipated reduction in tetracycline systemic absorption due to an interaction with bismuth and/or bismuth subsalicylate tablet excipients (calcium carbonate), the relative contribution of systemic versus local antimicrobial activity against H. pylori for these agents has not been established.

7. What are possible or reasonably likely side effects of Bismuth Subsalicylate Chewable Tablets/Metronidazole Tablets/Tetracycline Hydrochloride Capsules?
Adverse reactions associated with the individual components of Bismuth Subsalicylate Chewable Tablets/Metronidazole Tablets/Tetracycline Hydrochloride Capsules have been well described and are included in the Package Insert. The most common adverse reactions (≥1.5%) are nausea (12.0%), diarrhea (6.8%), abdominal pain (6.8%), melena (3.0%), upper respiratory infection (2.3%), constipation (1.9%), anorexia (1.5%), asthenia (1.5%), vomiting (1.5%), discolored tongue (1.5%), headache (1.5%), dyspepsia (1.5%), and dizziness (1.5%). The majority of the events were related to the gastrointestinal tract, were reversible, and usually did not lead to discontinuation of therapy. Some other possible adverse reactions include:
a. Bismuth subsalicylate may cause a temporary and harmless darkening of the tongue and/or black stool. This should not be confused with melena (blood in the stool).
b. Metallic taste in the mouth
c. Temporary darkening of the urine (rare)
d. Sore mouth
e. Yeast infections in women
f. Tooth enamel discoloration and hypoplasia (spots on teeth). Use of tetracycline during tooth development (second and third trimesters of pregnancy, infancy, and childhood to 8 years) may cause permanent discoloration of the teeth.
g. Superinfections. Use of antibiotics may result in overgrowth of nonsusceptible organisms, including fungi.
h. Central Nervous Effects. All of the components of Bismuth Subsalicylate Chewable Tablets/Metronidazole Tablets/Tetracycline Hydrochloride Capsules have been associated with central nervous effects such as seizures, peripheral neuropathy, neurotoxicity and intracranial hypertension.
As with most medications, rare but serious side effects have been reported with the use of the components contained in Bismuth Subsalicylate Chewable Tablets/Metronidazole Tablets/Tetracycline Hydrochloride Capsules. (See Package Insert.) Patients should be instructed to report any unusual symptoms to their pharmacist or prescriber. Patients may also report side effects to FDA at 1-800-FDA-1088.

8. General Information about the safe and effective use of Bismuth Subsalicylate Chewable Tablets/Metronidazole Tablets/Tetracycline Hydrochloride Capsules
Medicines are sometimes prescribed for purposes other than those listed. If your patients have any questions or concerns about Bismuth Subsalicylate Chewable Tablets/Metronidazole Tablets/Tetracycline Hydrochloride Capsules, ask them to consult their doctor. Tell your patients not to use Bismuth Subsalicylate Chewable Tablets/Metronidazole Tablets/Tetracycline Hydrochloride Capsules for a condition for which it was not prescribed. Tell them not to share their medicine with other people.

Bismuth Subsalicylate Chewable Tablets, 262.4 mg are manufactured by:
WES Pharma Inc
Westminster, MD 21157 USA

Metronidazole Tablets USP, 250 mg are manufactured by:
Watson Pharma Private Limited
Verna, Salcette Goa 403 722 INDIA

Tetracycline Hydrochloride Capsules USP, 500 mg are manufactured by:
Watson Pharma Private Limited
Verna, Salcette Goa 403 722 INDIA

for
Ailex Pharmaceuticals, LLC
Lenexa, KS 66219 USA

Rev.: 08/2018